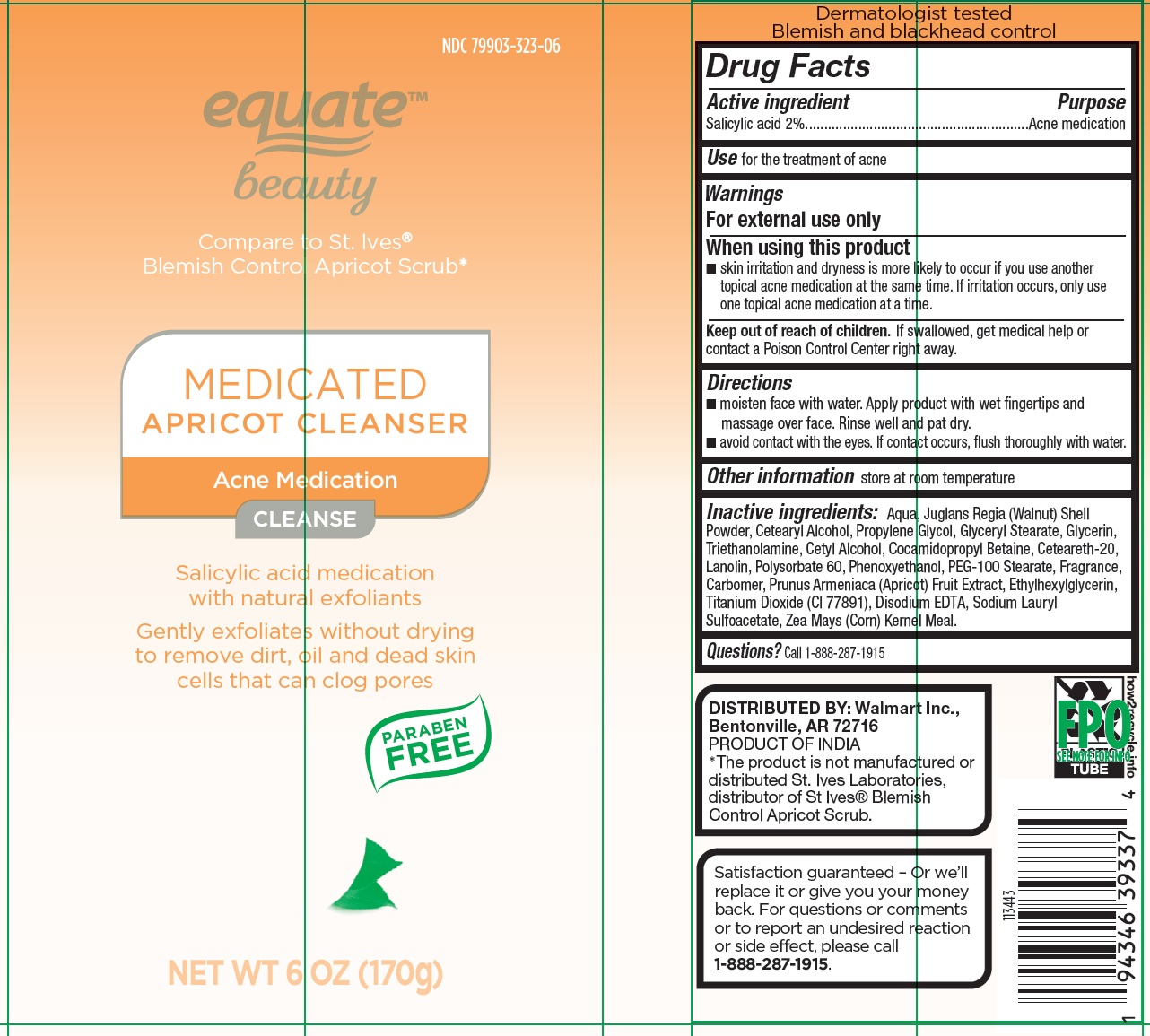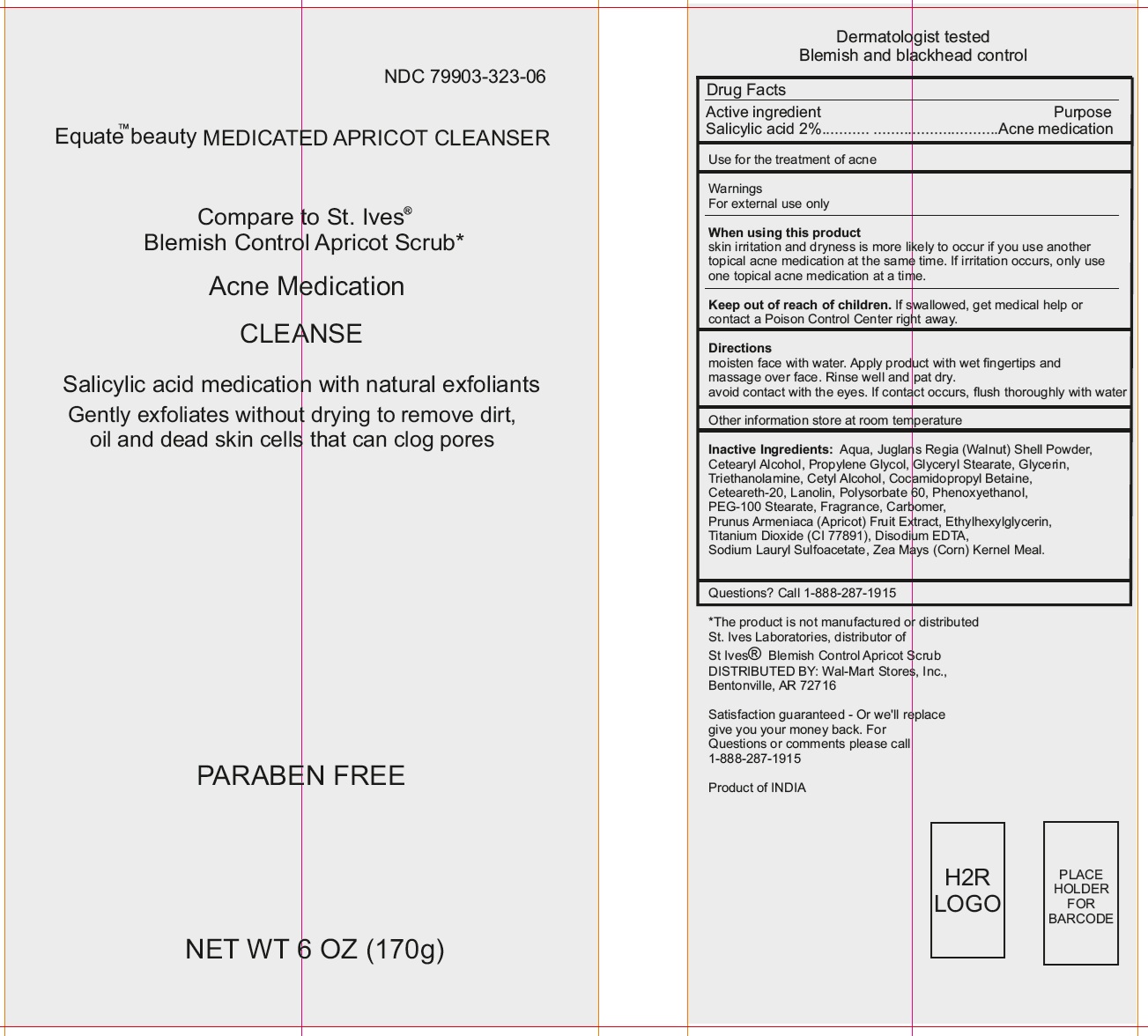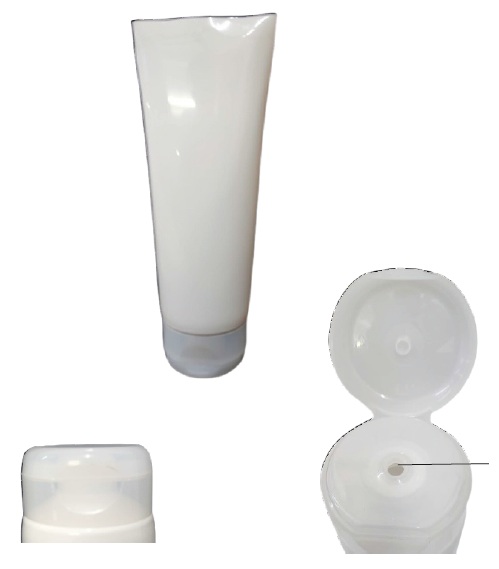 DRUG LABEL: Equate Beauty Medicated Apricot Cleanser Acne Medication
NDC: 79903-323 | Form: CREAM
Manufacturer: WALMART INC.
Category: otc | Type: HUMAN OTC DRUG LABEL
Date: 20250114

ACTIVE INGREDIENTS: SALICYLIC ACID 20 mg/1 g
INACTIVE INGREDIENTS: WATER; JUGLANS REGIA SHELL; CETEARYL ALCOHOL; PROPYLENE GLYCOL; GLYCERYL STEARATE; GLYCERIN; TRIETHANOLAMINE; CETYL ALCOHOL; COCAMIDOPROPYL BETAINE; CETEARETH-20; LANOLIN; POLYSORBATE 60; PHENOXYETHANOL; PEG-100 STEARATE; CARBOMER HOMOPOLYMER, UNSPECIFIED TYPE; APRICOT; ETHYLHEXYLGLYCERIN; TITANIUM DIOXIDE; EDETATE DISODIUM; SODIUM LAURYL SULFOACETATE; CORN GRAIN

Equate Beauty Medicated Apricot Cleanser Acne Medication

Active ingredient

Salicylic acid 2%

Purpose

Acne medication

Use

for the treatment of acne

Warnings

For external use only

When using this product

- skin irritation and dryness is more likely to occur if you use another topical acne medication at the same time. If irritation occurs, only use one topical acne medication at a time.

Keep out of reach of children.

If swallowed, get medical help or contact a Poison Control Center right away.

Directions

- moisten face with water. Apply product with wet fingertips and massage over face. Rinse well and pat dry.
- avoid contact with the eyes. If contact occurs, flush thoroughly with water.

Other information

store at room temperature

Inactive ingredients:

Aqua, Juglans Regia (Walnut) Shell Powder, Cetearyl Alcohol, Propylene Glycol, Glyceryl Stearate, Glycerin, Triethanolamine, Cetyl Alcohol, Cocamidopropyl Betaine, Ceteareth-20, Lanolin, Polysorbate 60, Phenoxyethanol, PEG-100 Stearate, Fragrance, Carbomer, Prunus Armeniaca (Apricot) Fruit Extract, Ethylhexylglycerin, Titanium Dioxide (CI 77891), Disodium EDTA, Sodium Lauryl Sulfoacetate, Zea Mays (Corn) Kernel Meal.

Questions?

Call 1-888-287-1915